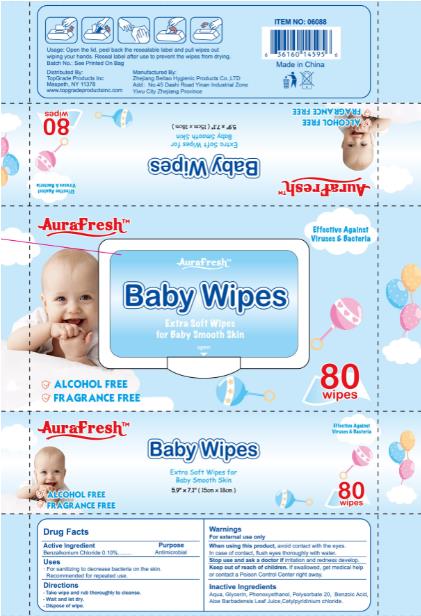 DRUG LABEL: Baby Wipes
NDC: 76906-005 | Form: CLOTH
Manufacturer: Zhejiang BeiTao Hygienic Products Co., Ltd.
Category: otc | Type: HUMAN OTC DRUG LABEL
Date: 20241222

ACTIVE INGREDIENTS: BENZALKONIUM CHLORIDE 0.1 g/100 mL
INACTIVE INGREDIENTS: BENZOIC ACID; CETYLPYRIDINIUM CHLORIDE; PHENOXYETHANOL; POLYSORBATE 20; WATER; ALOE VERA LEAF; GLYCERIN

76906-005 baby wipes 0.1% Benzalkonium Chloride

Active Ingredient

Benzalkonium Chloride 0.1%

Purpose

Antiseptice Handwash

USE

For sanitizing to decrease bacteria on the skin.
Recommended for repeated use.

Warning

For external use only
When using this product, avoid contact with eyes. In case of contact, flush eyes thoroughly with water
Stop use and ask a doctor if irritation and redness develop.

Keep out of reach of children. If swallowed, get medical help
or contact a Poison Control Center right away.

Directions

Take wipe and rub thoroughly to cleanse

Wait and let dry

Dispose of wipe

Inactive ingredients

Aqua,Glycerin,Phenoxyethanol,Polysorbate 20,Benzoic Acid,Aloe Barbadensis Leaf Juice,Cetylpyridinium Chloride.

PACKAGE LABEL

80 piece NDC 76906-005-01